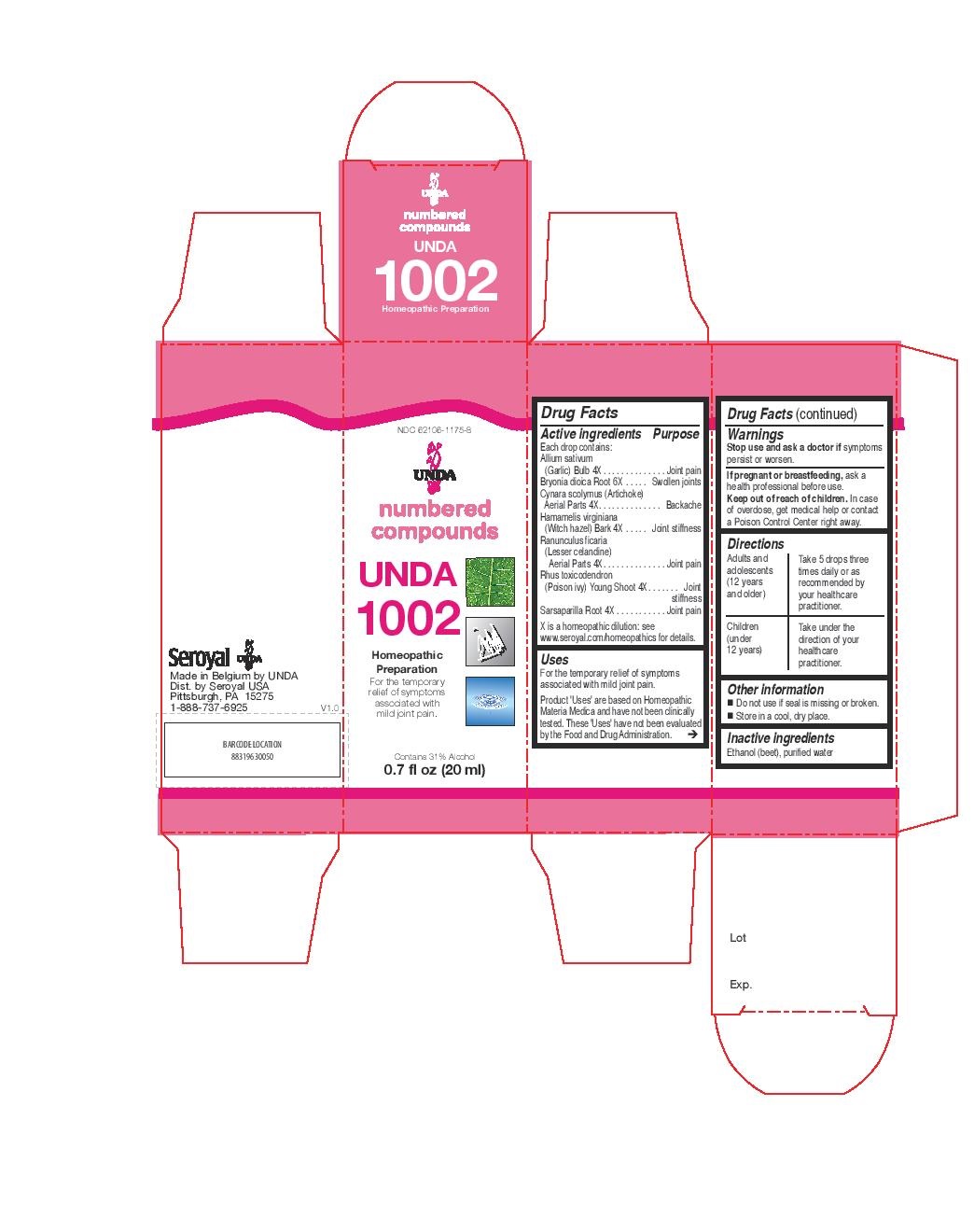 DRUG LABEL: UNDA 1002
NDC: 62106-1175 | Form: LIQUID
Manufacturer: Seroyal USA
Category: homeopathic | Type: HUMAN OTC DRUG LABEL
Date: 20221109

ACTIVE INGREDIENTS: RANUNCULUS FICARIA 4 [hp_X]/20 mL; SARSAPARILLA 4 [hp_X]/20 mL; GARLIC 4 [hp_X]/20 mL; CYNARA SCOLYMUS LEAF 4 [hp_X]/20 mL; HAMAMELIS VIRGINIANA ROOT BARK/STEM BARK 4 [hp_X]/20 mL; TOXICODENDRON PUBESCENS SHOOT 4 [hp_X]/20 mL; BRYONIA DIOICA ROOT 6 [hp_X]/20 mL
INACTIVE INGREDIENTS: ALCOHOL; WATER

UNDA 1002

Active ingredients
Each drop contains:
Allium sativum (Garlic) Bulb 4X
Bryonia dioica Root 6X
Cynara scolymus (Artichoke) Aerial Parts 4X
Hamamelis virginiana (Witch hazel) Bark 4X
Ranunculus ficaria (Lesser celandine) Aerial Parts 4X
Rhus toxicodendron (Poison ivy) Young Shoot 4X
Sarsaparilla Root 4X

Uses
For the temporary relief of symptoms associated with mild joint pain.

Warnings
Stop use and ask a doctor if symptoms persist or worsen.
If pregnant or breastfeeding, ask a health professional before use.
Keep out of reach of children. In case of overdose, get medical help or contact
a Poison Control Center right away.

Keep out of reach of children.

PREGNANCY OR BREAST FEEDING

If pregnant or breastfeeding, ask a health professional before use.

Stop use and ask a doctor if symptoms persist or worsen.

Other information
Do not use if seal is missing or broken.
Store in a cool, dry place.

Inactive ingredients
Ethanol (beet), purified water

Directions
Adults and adolescents (12 years and older)

Take 5 drops three times daily or as recommended by your healthcare practitioner.
Children (under 12 years)
Take under the direction of your healthcare practitioner.

Uses
For the temporary relief of symptoms associated with mild joint pain.

Directions
Adults and adolescents (12 years and older)

Take 5 drops three times daily or as recommended by your healthcare practitioner.
Children (under 12 years)
Take under the direction of your healthcare practitioner.

PACKAGE LABEL

NDC 62106-1175-8

UNDA

numbered compounds

UNDA 1002

Homeopathic Preparation

For the temporary relief of symptoms
associated with mild joint pain.

Contains 31% Alcohol
0.7 fl oz (20 ml)